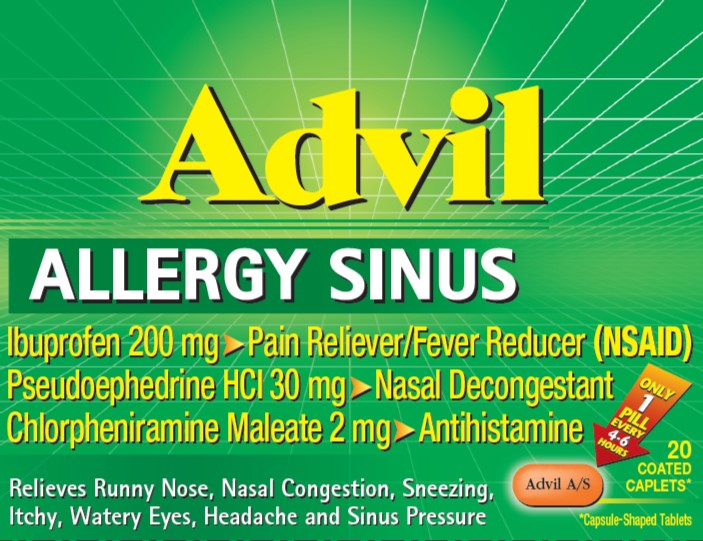 DRUG LABEL: ADVIL ALLERGY SINUS
NDC: 0573-0188 | Form: TABLET, COATED
Manufacturer: Haleon US Holdings LLC
Category: otc | Type: HUMAN OTC DRUG LABEL
Date: 20240620

ACTIVE INGREDIENTS: CHLORPHENIRAMINE MALEATE 2 mg/1 1; IBUPROFEN 200 mg/1 1; PSEUDOEPHEDRINE HYDROCHLORIDE 30 mg/1 1
INACTIVE INGREDIENTS: CARNAUBA WAX; STARCH, CORN; SILICON DIOXIDE; FD&C RED NO. 40; CROSCARMELLOSE SODIUM; FD&C YELLOW NO. 6; GLYCERYL DIBEHENATE; MICROCRYSTALLINE CELLULOSE; POLYDEXTROSE; HYPROMELLOSE, UNSPECIFIED; TITANIUM DIOXIDE; POLYETHYLENE GLYCOL, UNSPECIFIED

Drug Facts

Active ingredients (in each caplet)

Chlorpheniramine maleate 2 mg

Ibuprofen 200 mg (NSAID)*

Pseudoephedrine HCl 30 mg

*nonsteroidal anti-inflammatory drug

Purposes

Antihistamine

Pain reliever/fever reducer

Nasal decongestant

Uses

temporarily relieves these symptoms associated with hay fever or other upper respiratory allergies, and the common cold:

- runny nose
- itchy, watery eyes
- itching of the nose or throat
- sneezing
- nasal congestion
- sinus pressure
- headache
- minor aches and pains
- fever

Warnings

Allergy alert: Ibuprofen may cause a severe allergic reaction, especially in people allergic to aspirin. Symptoms may include:

- hives
- facial swelling
- asthma (wheezing)
- shock
- skin reddening
- rash
- blisters

If an allergic reaction occurs, stop use and seek medical help right away.

Stomach bleeding warning: This product contains an NSAID, which may cause severe stomach bleeding. The chance is higher if you:

- are age 60 or older
- have had stomach ulcers or bleeding problems
- take a blood thinning (anticoagulant) or steroid drug
- take other drugs containing prescription or nonprescription NSAIDs [aspirin, ibuprofen, naproxen, or others]
- have 3 or more alcoholic drinks every day while using this product
- take more or for a longer time than directed

Do not use

- in children under 12 years of age
- if you have ever had an allergic reaction to any other pain reliever/fever reducer
- right before or after heart surgery
- if you are now taking a prescription monoamine oxidase inhibitor (MAOI) (certain drugs for depression, psychiatric, or emotional conditions, or Parkinson's disease), or for 2 weeks after stopping the MAOI drug. If you do not know if your prescription drug contains an MAOI, ask a doctor or pharmacist before taking this product.

Ask a doctor before use if

- you have a breathing problem such as emphysema or chronic bronchitis
- stomach bleeding warning applies to you
- you have problems or serious side effects from taking pain relievers or fever reducers
- you have a history of stomach problems, such as heartburn
- you have high blood pressure, heart disease, liver cirrhosis, kidney disease, asthma, thyroid disease, diabetes, glaucoma, trouble urinating due to an enlarged prostate gland, or had a stroke
- you are taking a diuretic

Ask a doctor or pharmacist before use if you are

- under a doctor's care for any serious condition
- taking sedatives or tranquilizers
- taking any other product that contains pseudoephedrine, chlorpheniramine or any other nasal decongestant or antihistamine
- taking aspirin for heart attack or stroke, because ibuprofen may decrease this benefit of aspirin
- taking any other drug

When using this product

- take with food or milk if stomach upset occurs
- avoid alcoholic drinks
- be careful when driving a motor vehicle or operating machinery
- drowsiness may occur
- alcohol, sedatives, and tranquilizers may increase drowsiness

Stop use and ask a doctor if

- you experience any of the following signs of stomach bleeding:
  - feel faint
  - vomit blood
  - have bloody or black stools
  - have stomach pain that does not get better
- you have symptoms of heart problems or stroke:
  - chest pain
  - trouble breathing
  - weakness in one part or side of body
  - slurred speech
  - leg swelling
- fever gets worse or lasts more than 3 days
- nasal congestion lasts for more than 7 days
- redness or swelling is present in the painful area
- you get nervous, dizzy, or sleepless
- symptoms continue or get worse
- any new symptoms appear

Directions

- do not take more than directed
- the smallest effective dose should be used
- adults: take 1 caplet every 4-6 hours while symptoms persist.
- do not take more than 6 caplets in any 24-hour period, unless directed by a doctor
- children under 12 years of age: do not use

Other information

- read all warnings and directions before use. Keep carton.
- store at 20-25°C (68-77°F)
- avoid excessive heat above 40°C (104°F)

Inactive ingredients

carnauba wax, colloidal silicon dioxide, corn starch, croscarmellose sodium, FD&C red no. 40 aluminum lake, FD&C yellow no. 6 aluminum lake, glyceryl behenate, hypromellose, microcrystalline cellulose, pharmaceutical ink, polydextrose, polyethylene glycol, pregelatinized starch, silicon dioxide, titanium dioxide

Questions or comments?

Call weekdays from 9 AM to 5 PM ESTat 1-800-88-ADVIL

Additional Information

READ AND KEEP CARTON FOR COMPLETE
WARNINGS AND INFORMATION

For most recent product information,

visit www.advil.com

Product inside sealed in plastic blister with foil backing.

Do Not Use if plastic blister or foil barrier is broken.

PRINCIPAL DISPLAY PANEL

Advil

ALLERGY SINUS

Ibuprofen 200 mg ➤ Pain Reliever/Fever Reducer (NSAID)
Pseudoephedrine HCl 30 mg ➤ Nasal Decongestant
Chlorpheniramine Maleate 2 mg ➤ Antihistamine

Relieves Runny Nose, Nasal Congestion, Sneezing,
Itchy, Watery Eyes, Headache and Sinus Pressure

ONLY
1
PILL
EVERY
4-6
HOURS

Advil
A/S

20 COATED CAPLETS*

*Capsule-Shaped Tablets

PAA148681 Carton